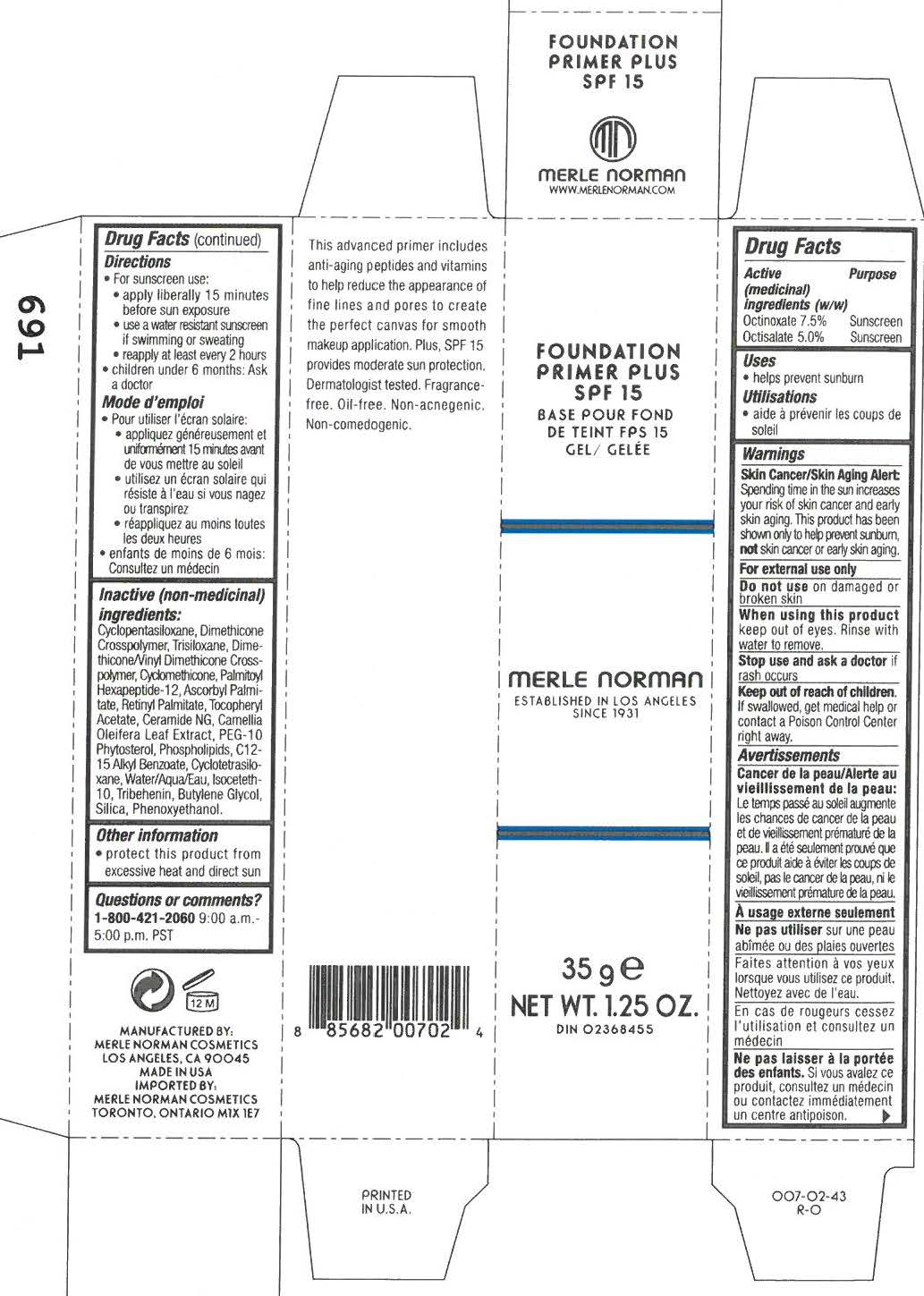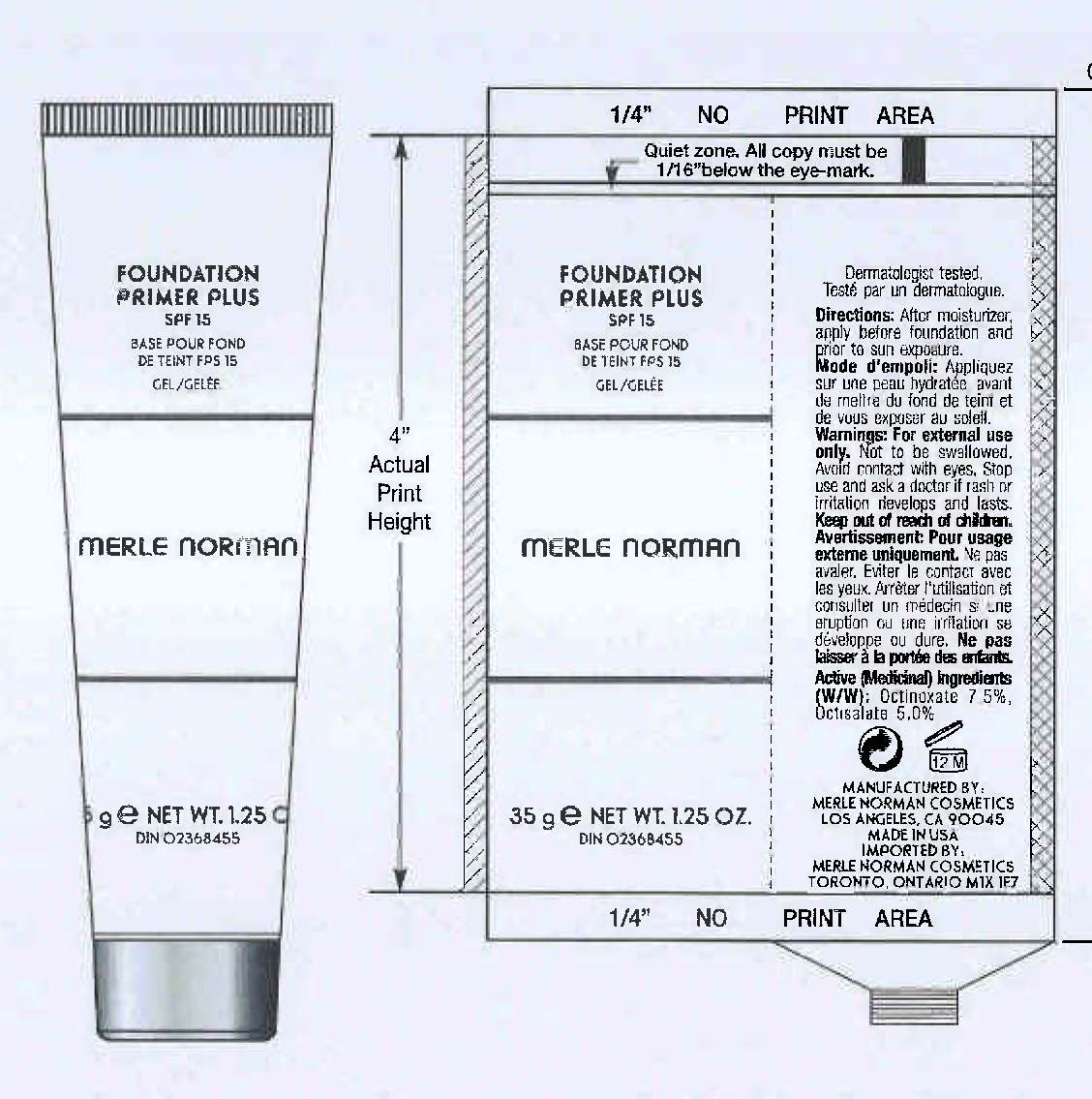 DRUG LABEL: Foundation Primer Plus SPF 15
NDC: 57627-108 | Form: CREAM
Manufacturer: Merle Norman Cosmetics, Inc
Category: otc | Type: HUMAN OTC DRUG LABEL
Date: 20251119

ACTIVE INGREDIENTS: OCTINOXATE 2.63 g/35 g; OCTISALATE 1.75 g/35 g
INACTIVE INGREDIENTS: CYCLOMETHICONE 5; TRISILOXANE; CYCLOMETHICONE 6; PALMITOYL TRIPEPTIDE-1; ASCORBYL PALMITATE; VITAMIN A PALMITATE; CERAMIDE 2; CAMELLIA OLEIFERA LEAF; PEG-10 RAPESEED STEROL; ALKYL (C12-15) BENZOATE; TRIBEHENIN; BUTYLENE GLYCOL; SILICON DIOXIDE; PHENOXYETHANOL

Foundation Primer Plus SPF 15

Active ingredients Purpose

OCTINOXATE 7.5% sunscreen

OCTISALATE 5.0% sunscreen

PURPOSE

Uses Helps Prevent Sunburn

Keep out of reach of children. If swallowed, get medical help or contact a Poison Control Center right away.

Stop use and ask a doctor if rash occurs and persists

Warnings

Skin Cancer/Skin Aging Alert

Spending time in the sun increases your risk of skin cancer and early skin aging. This product has been shown only to prevent sunburn, not skin canceror early skin aging.

For external use only.

Do not use on damaged or Broken skin

When using this product

keep out of eyes. Rinse with water to remove.

Directions

For Sunscreen use:

Apply Liberally 15 minutes before sun exposure
Use a water resistant sunscreen if swimming or sweating
Reapply at least every 2 hours
Children under 6 months: Ask a doctor

Inactive ingredients

Cyclopentasiloxane, Dimethicone Crosspolymer, Trisiloxane, Dimethicone/Vinyl Dimethicone Crosspolymer, Cyclomethicone, Palmitoyl Oligopeptide, Ascorbyl Palmitate, Retinyl Palmitate, Tocopheryl Acetate, Ceramide 2 , Camellia Oleifera Leaf Extract, PEG-10 Rapeseed Sterol, Phospholipids, C12-15 Alkyl Benzoate, Cyclotetrasiloxane, Water (Aqua), Isoceteth-10, Tribehenin, Butylene Glycol, Silica, Phenoxyethanol.

PACKAGE LABEL

Foundation Primer Plus

SPF 15

Merle Norman

35g Net Wt. 1.25 OZ